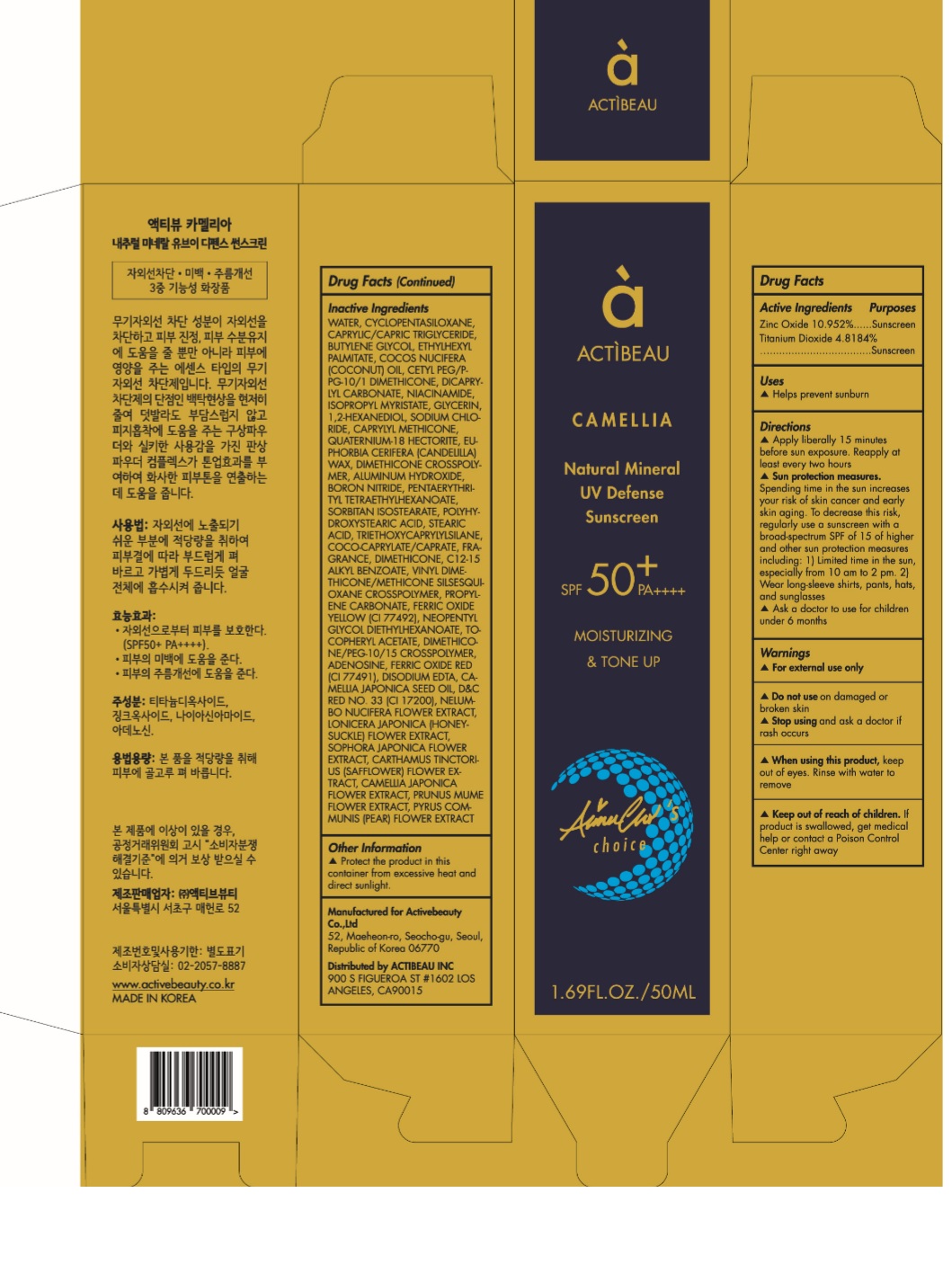 DRUG LABEL: ACTIBEAU Camellia Natural Mineral UV Defense Sunscreen
NDC: 73016-003 | Form: CREAM
Manufacturer: ACTIVEBEUTY CO.,LTD
Category: otc | Type: HUMAN OTC DRUG LABEL
Date: 20190403

ACTIVE INGREDIENTS: ZINC OXIDE 109.52 mg/1 mL; TITANIUM DIOXIDE 48.187 mg/1 mL
INACTIVE INGREDIENTS: WATER; CYCLOMETHICONE 5; MEDIUM-CHAIN TRIGLYCERIDES; BUTYLENE GLYCOL; ETHYLHEXYL PALMITATE; COCONUT OIL; CETYL PEG/PPG-10/1 DIMETHICONE (HLB 2); DICAPRYLYL CARBONATE; NIACINAMIDE; ISOPROPYL MYRISTATE; GLYCERIN; 1,2-HEXANEDIOL; SODIUM CHLORIDE; CAPRYLYL TRISILOXANE; QUATERNIUM-18 HECTORITE; CANDELILLA WAX; DIMETHICONE CROSSPOLYMER (450000 MPA.S AT 12% IN CYCLOPENTASILOXANE); ALUMINUM HYDROXIDE; BORON NITRIDE; PENTAERYTHRITYL TETRAETHYLHEXANOATE; SORBITAN ISOSTEARATE; POLYHYDROXYSTEARIC ACID (2300 MW); STEARIC ACID; TRIETHOXYCAPRYLYLSILANE; COCO-CAPRYLATE/CAPRATE; DIMETHICONE; ALKYL (C12-15) BENZOATE; VINYL DIMETHICONE/METHICONE SILSESQUIOXANE CROSSPOLYMER; PROPYLENE CARBONATE; FERRIC OXIDE YELLOW; NEOPENTYL GLYCOL DIETHYLHEXANOATE; .ALPHA.-TOCOPHEROL ACETATE; ADENOSINE; FERRIC OXIDE RED; EDETATE DISODIUM ANHYDROUS; CAMELLIA JAPONICA SEED OIL; D&C RED NO. 33; NELUMBO NUCIFERA FLOWER; LONICERA JAPONICA FLOWER; STYPHNOLOBIUM JAPONICUM FLOWER; SAFFLOWER; CAMELLIA JAPONICA FLOWER; PRUNUS MUME FLOWER; PYRUS COMMUNIS FLOWER

73016-003

ACTIVE INGREDIENT

Zinc Oxide 10.952%
Titanium Dioxide 4.8184%

PURPOSE

Sunscreen

INDICATIONS AND USAGE

Helps prevent sunburn

DOSAGE AND ADMINISTRATION

Apply liberally 15 minutes before sun exposure. Reapply at least every two hours

WARNINGS

For external use only.
Do not use on damaged or broken skin.
When using this product, keep out of eyes. Rinse with water to remove.
Stop using and ask a doctor if rash occurs.

KEEP OUT OF REACH OF CHILDREN

Keep out of reach of the children. If product is swallowed, get medical help or contact a poison control center right away.

INACTIVE INGREDIENT

WATER, CYCLOPENTASILOXANE, CAPRYLIC/CAPRIC TRIGLYCERIDE, BUTYLENE GLYCOL, ETHYLHEXYL PALMITATE, COCOS NUCIFERA (COCONUT) OIL, CETYL PEG/PPG-10/1 DIMETHICONE, DICAPRYLYL CARBONATE, NIACINAMIDE, ISOPROPYL MYRISTATE, GLYCERIN, 1,2-HEXANEDIOL, SODIUM CHLORIDE, CAPRYLYL METHICONE, QUATERNIUM-18 HECTORITE, EUPHORBIA CERIFERA (CANDELILLA) WAX, DIMETHICONE CROSSPOLYMER, ALUMINUM HYDROXIDE, BORON NITRIDE, PENTAERYTHRITYL TETRAETHYLHEXANOATE, SORBITAN ISOSTEARATE, POLYHYDROXYSTEARIC ACID, STEARIC ACID, TRIETHOXYCAPRYLYLSILANE, COCO-CAPRYLATE/CAPRATE, FRAGRANCE, DIMETHICONE, C12-15 ALKYL BENZOATE, VINYL DIMETHICONE/METHICONE SILSESQUIOXANE CROSSPOLYMER, PROPYLENE CARBONATE, FERRIC OXIDE YELLOW (CI 77492), NEOPENTYL GLYCOL DIETHYLHEXANOATE, TOCOPHERYL ACETATE, DIMETHICONE/PEG-10/15 CROSSPOLYMER, ADENOSINE, FERRIC OXIDE RED (CI 77491), DISODIUM EDTA, CAMELLIA JAPONICA SEED OIL, D&C RED NO. 33 (CI 17200), NELUMBO NUCIFERA FLOWER EXTRACT, LONICERA JAPONICA (HONEYSUCKLE) FLOWER EXTRACT, SOPHORA JAPONICA FLOWER EXTRACT, CARTHAMUS TINCTORIUS (SAFFLOWER) FLOWER EXTRACT, CAMELLIA JAPONICA FLOWER EXTRACT, PRUNUS MUME FLOWER EXTRACT, PYRUS COMMUNIS (PEAR) FLOWER EXTRACT